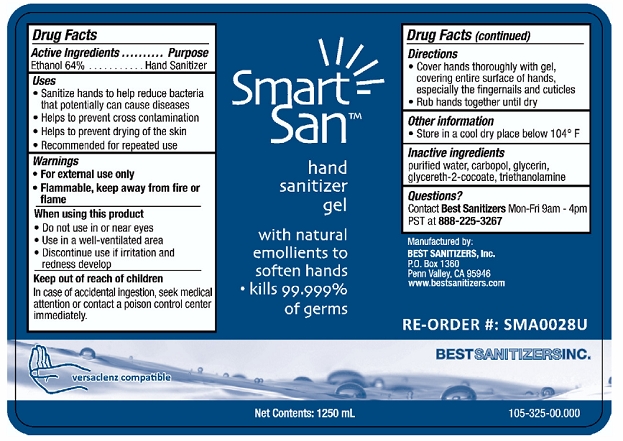 DRUG LABEL: Smart San Hand Sanitizer
NDC: 59900-116 | Form: LIQUID
Manufacturer: Best Sanitizers, Inc
Category: otc | Type: HUMAN OTC DRUG LABEL
Date: 20100425

ACTIVE INGREDIENTS: Ethanol 693 g/1000 mL

Drug Facts

Active Ingredient

Ethanol 64%

Purpose

Hand Sanitizer

Uses

- Sanitize hand to help reduce bacteria that potentially can cause diseases
- Helps to prevent cross contamination
- Helps to prevent drying of the skin
- Recommended for repeated use

Warnings

- For external use only
- Flammable, keep away from fire or flame

When using this product

- Do not use in or near eyes
- Use in a well-ventilated area
- Discontinue use if irritation and redness develop

Keep out of reach of children

In case of accidental ingestion, seek medical attention or contact a poison control center immediately.

Directions

- Cover hands thoroughly with gel, covering entire surface of hands, especially the fingernails and cuticles
- Rub hands together until dry

Other Information

- Store in a cool dry place below 104° F

Inactive ingredients

purified water, carbopol, glycerin, glycereth-2-cocate, triethanolamine

Questions?

Contact Best Sanitizers Mon-Fri 9am - 4pm PST at 888-225-3267

Principal Display Panel

NDC 59900-116-01

NDC 59900-116-02

NDC 59900-116-03

NDC 59900-116-04

NDC 59900-116-06

Smart San™ hand Sanitizer Gel